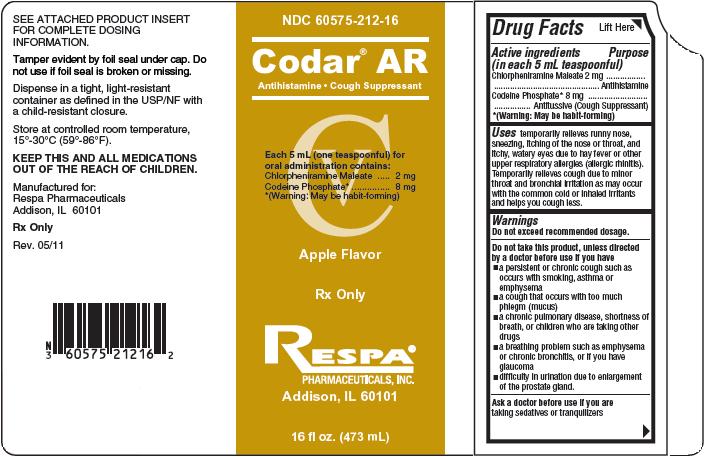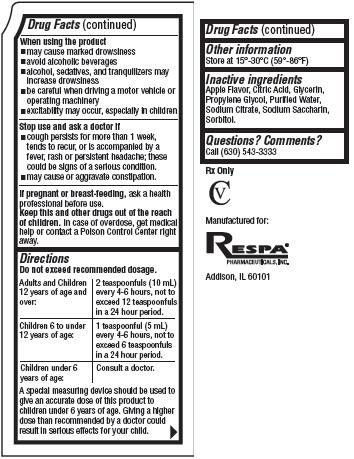 DRUG LABEL: Codar
NDC: 60575-212 | Form: LIQUID
Manufacturer: Respa Pharmaceuticals, Inc.
Category: otc | Type: HUMAN OTC DRUG LABEL
Date: 20110620
DEA Schedule: CV

ACTIVE INGREDIENTS: Chlorpheniramine Maleate 2 mg/5 mL; Codeine Phosphate 8 mg/5 mL
INACTIVE INGREDIENTS: Citric Acid; Propylene Glycol; Water; Sodium Citrate; Saccharin Sodium; Sorbitol

Codar AR

Drug Facts

Active ingredients
(in each 5 mL teaspoonful)
Chlorpheniramine Maleate 2 mg
Codeine Phosphate* 8 mg
*(Warning: May be habit-forming)

Purpose

Antihistamine
Antitussive (Cough Suppressant)

Uses

temporarily relieves runny nose, sneezing, itching of the nose or throat, and itchy watery eyes due to hay fever or other upper respiratory allergies (allergic rhinitis). Temporarily relieves cough due to minor throat and bronchial irritation as may occur with the common cold or inhaled irritants and helps you cough less.

Warnings

Do not exceed recommended dosage.

Do not take this product, unless directed by a doctor before use if you have

- a persistent or chronic cough such as occurs with smoking, asthma or emphysema
- a cough that occurs with too much phlegm (mucus)
- a chronic pulmonary disease, shortness of breath, or children who are taking other drugs
- a breathing problem such as emphysema or chronic bronchitis, or if you have glaucoma
- difficulty in urination due to enlargement of the prostate gland.

Ask a doctor before use if you are

taking sedatives or tranquilizers

When using this product

- may cause marked drowsiness
- avoid alcoholic beverages
- alcohol, sedatives, and tranquilizers may increase drowsiness
- be careful when driving a motor vehicle or operating machinery
- excitability may occur, especially in children

Stop use and ask a doctor if

- cough persists for more than 1 week, tends to recur, or is accompanied by a fever, rash or persistent headache; these could be signs of a serious condition.
- may cause or aggravate constipation.

If pregnant or breast-feeding,

ask a health professional before use.

Keep this and other drugs out of the reach of children.

In case of overdose, get medical help or contact a Poison Control Center right away.

Directions

Do not exceed recommended dosage.

Adults and Children 12 years of age and over: | 2 teaspoonfuls (10 mL) every 4-6 hours, not to exceed 12 teaspoonfuls in a 24 hour period.
Children 6 to under 12 years of age: | 1 teaspoonful (5 mL) every 4-6 hours, not to exceed 6 teaspoonfuls in a 24 hour period.
Children under 6 years of age: | Consult a doctor.

A special measuring device should be used to give an accurate dose of this product to children under 6 years of age. Giving a higher dose than recommended by a doctor could result in serious effects for your child.

Other information

Store at 15°- 30°C (59°- 86°F)

Inactive ingredients

Apple Flavor, Citric Acid, Glycerin, Propylene Glycol, Purified Water, Sodium Citrate, Sodium Saccharin, Sorbitol.

Questions? Comments?

Call (630) 543-3333
Rx Only
CV
Manufactured for:
RESPA
PHARMACEUTICALS, INC.
Addision, IL 60101

Product Packaging

The packaging below represents the labeling currently used:
Principal display panel and side panel for 473 mL label:
NDC 60575-212-16
_____________________________________________
Codar AR
Antihistamine / Cough Suppressant
_____________________________________________
Each 5 mL (one teaspoonful) for oral
administration contains:
Chloropheniramine Maleate................................2 mg
Codeine Phosphate*..........................................8 mg
*(Warning: May be habit-forming)
CV
Apple Flavor
Rx Only
RESPA
PHARMACEUTICALS, INC.
Addision, IL 60101
16 fl oz. (473 mL)
SEE ATTACHED PRODUCT INSERT FOR COMPLETE
DOSING INFORMATION.
Tamper evident by foil seal under cap. Do not use if foil seal
is broken or missing.
Dispense in a tight, light-resistant container as defined in the
USP/NF with a child-resistant closure.
Store at controlled room temperature, 15°- 30°C (59°- 86°F).
KEEP THIS AND ALL MEDICATIONS OUT OF THE
REACH OF CHILDREN.
Manufactured for:
Respa Pharmaceuticals
Addison, IL 60101
Rx Only
Rev. 05/11